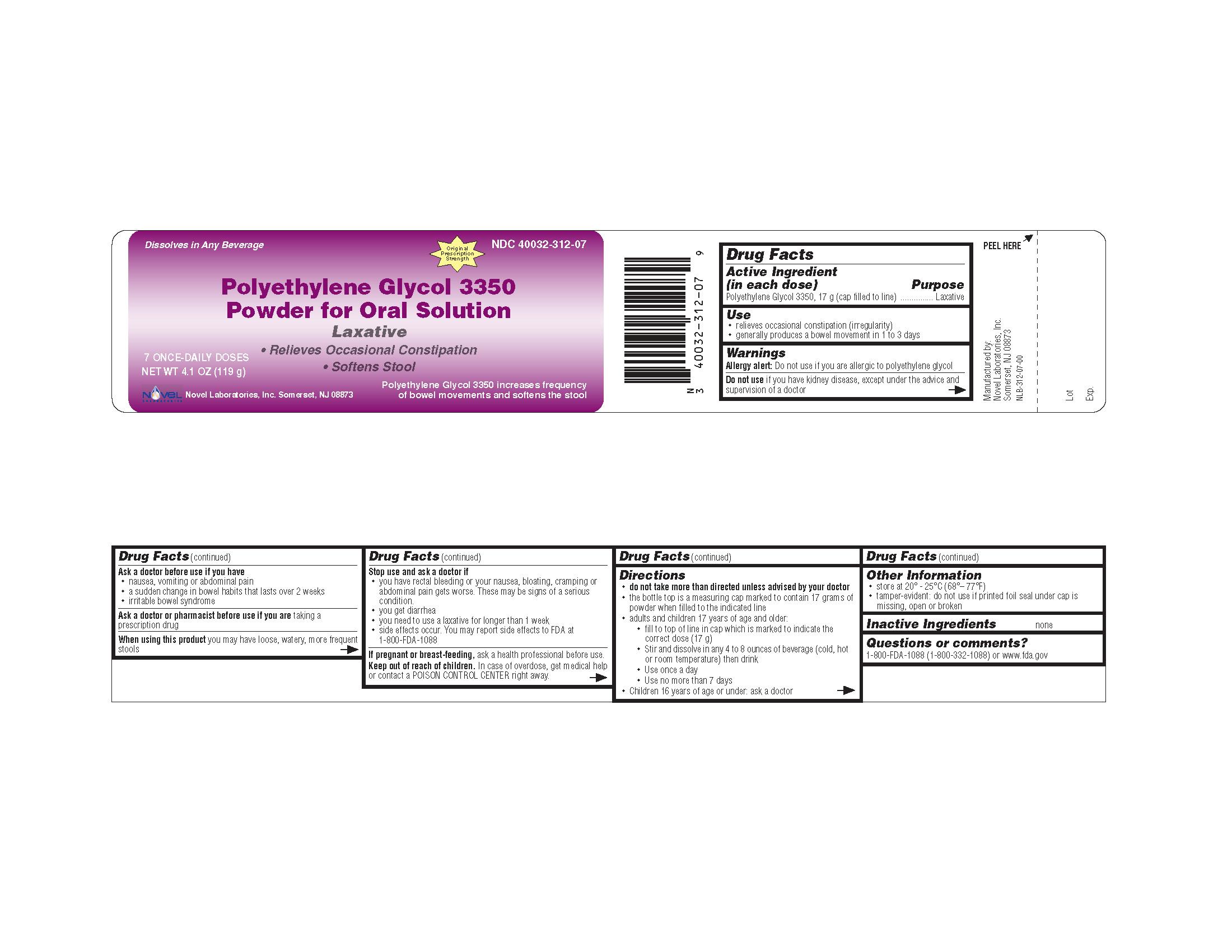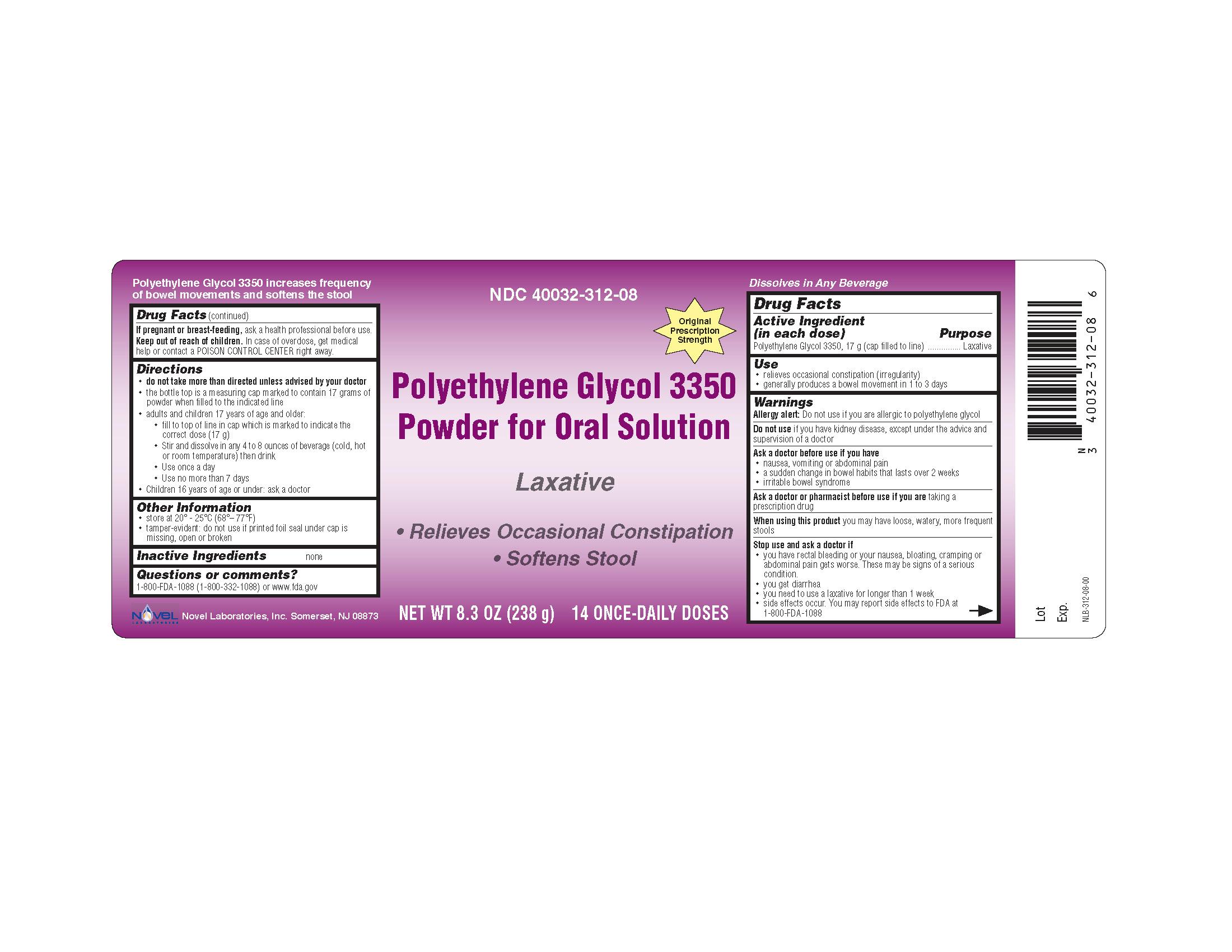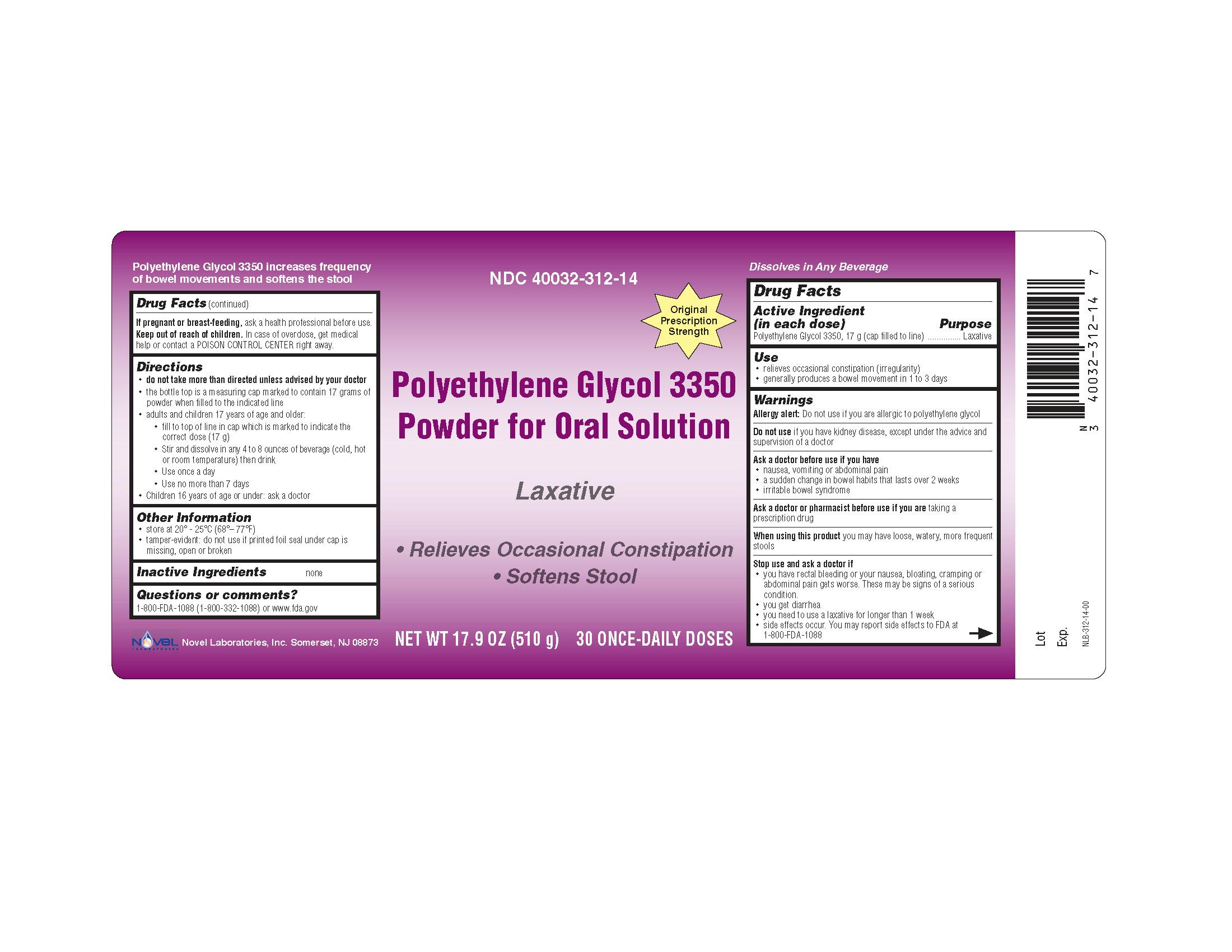 DRUG LABEL: Polyethylene Glycol-3350
NDC: 40032-312 | Form: POWDER, FOR SOLUTION
Manufacturer: Novel Laboratories, Inc.
Category: otc | Type: HUMAN OTC DRUG LABEL
Date: 20091006

ACTIVE INGREDIENTS: POLYETHYLENE GLYCOL 3350 17 g/17 g

Polyethylene Glycol 3350, Powder for Oral Solution

Drug Facts

OTC - ACTIVE INGREDIENT

Active Ingredient (in each dose)..........................................Purpose

Polyethylene Glycol 3350, 17 g (cap filled to line).....................Laxative

Use

- relieves occasional constipation (irregularity)
- generally produces a bowel movement in 1 to 3 days

WARNINGS

Allergy alert: Do not use if you are allergic to polyethylene glycol

OTC - DO NOT USE

Do not use if you have kidney disease, except under the advice and supervision of a doctor

OTC - ASK DOCTOR

Ask a doctor before use if you have

- nausea, vomiting or abdominal pain
- a sudden change in bowel habits that lasts over 2 weeks
- irritable bowel syndrome

OTC - ASK DOCTOR/PHARMACIST

Ask a doctor or pharmacist before use if you are taking a prescription drug

OTC - WHEN USING

When using this product you may have loose, watery, more frequent stools

OTC - STOP USE

Stop use and ask a doctor if

- you have rectal bleeding or your nausea, bloating, cramping or abdominal pain gets worse. These may be signs of a serious condition.
- you get diarrhea
- you need to use a laxative for longer than 1 week
- side effects occur. You may report side effects to FDA at 1-800-FDA-1088

Drug Facts (continued)

OTC - PREGNANCY OR BREAST FEEDING

If pregnant or breast-feeding, ask a health professional before use.

OTC - KEEP OUT OF REACH OF CHILDREN

Keep out of reach of children. In case of overdose, get medical help or contact a POISON CONTROL CENTER right away.

Directions

- do not take more than directed unless advised by your doctor
- the bottle top is a measuring cap marked to contain 17 grams of powder when filled to the indicated line.
- adults and children 17 years of age and older:
  - fill to top of line in cap which is marked to indicate the correct dose (17 g)
  - stir and dissolve in any 4 to 8 ounces of beverage (cold, hot or room temperature) then drink
  - use once a day
  - use no more than 7 days
- children 16 years of age or under: ask a doctor

Other Information

- store at 20° - 25°C (68°– 77°F)
- tamper-evident: do not use if printed foil seal under cap is missing, open or broken

INACTIVE INGREDIENT

Inactive Ingredients none

OTC - QUESTIONS

Questions or comments?

1-800-FDA-1088 (1-800-332-1088) or www.fda.gov